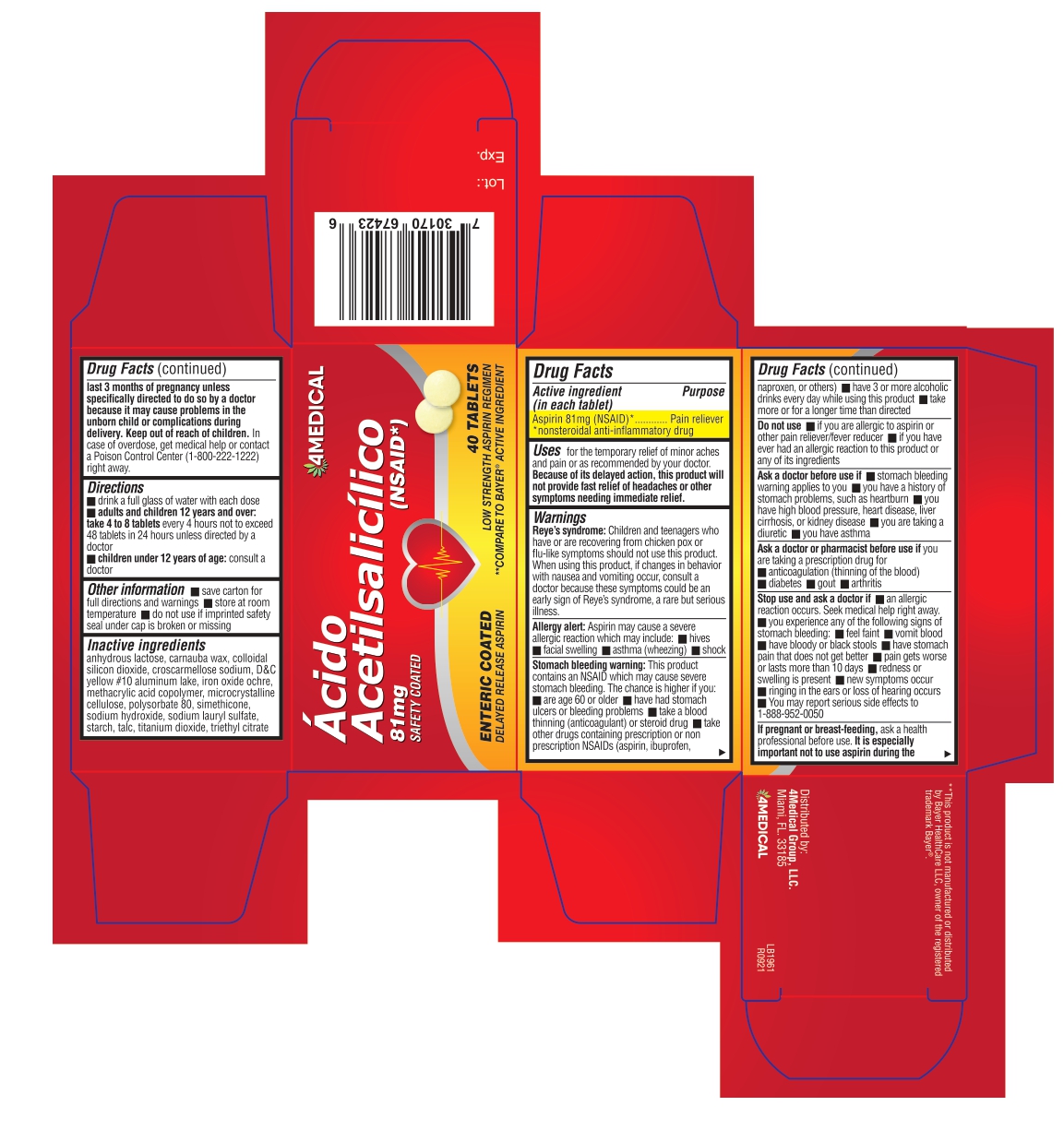 DRUG LABEL: Acido Acetilsalicilico
NDC: 83337-232 | Form: TABLET, COATED
Manufacturer: 4Medical Group LLC
Category: otc | Type: HUMAN OTC DRUG LABEL
Date: 20230706

ACTIVE INGREDIENTS: ASPIRIN 81 mg/1 1
INACTIVE INGREDIENTS: POLYSORBATE 80; TRIETHYL CITRATE; SILICON DIOXIDE; TALC; ANHYDROUS LACTOSE; DIMETHICONE; SODIUM LAURETH SULFATE; CARNAUBA WAX; CROSCARMELLOSE SODIUM; BROWN IRON OXIDE; MICROCRYSTALLINE CELLULOSE; STARCH, CORN; TITANIUM DIOXIDE; SODIUM HYDRIDE; D&C YELLOW NO. 10 ALUMINUM LAKE; METHACRYLIC ACID - METHYL METHACRYLATE COPOLYMER (1:1)

OTC Label - Aspirin - Allegiant Health